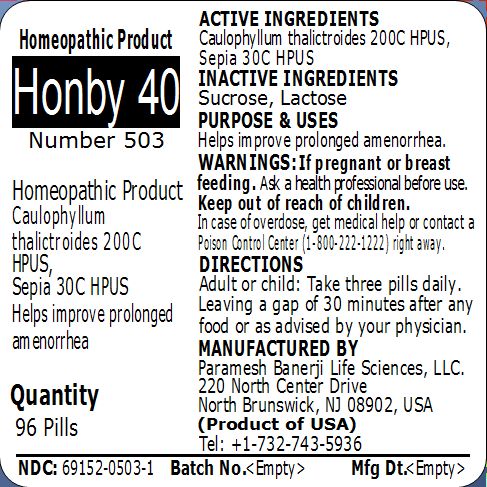 DRUG LABEL: Honby 40 Number 503
NDC: 69152-0503 | Form: PELLET
Manufacturer: Paramesh Banerji Life Sciences LLC
Category: homeopathic | Type: HUMAN OTC DRUG LABEL
Date: 20150302

ACTIVE INGREDIENTS: CAULOPHYLLUM THALICTROIDES ROOT 200 [hp_C]/1 1; SEPIA OFFICINALIS JUICE 30 [hp_C]/1 1
INACTIVE INGREDIENTS: LACTOSE; SUCROSE

Active Ingredients

Caulophyllum thalictroides 200C HPUS, Sepia 30C HPUS

Inactive Ingredients

Sucrose, Lactose

Purpose

Helps improve prolonged amenorrhea

Uses

Helps improve prolonged amenorrhea

Warnings

If pregnant or breast feeding ask a health professional before use.

Keep out of reach of children. In case of overdose, get medical help or contact a Poison Control Center (1-800-222-1222) right away.

Direction

Adult or child: Take three pills daily. Leaving a gap of 30 minutes after any food or as advised by your physician.

Manufactured by

Paramesh Banerji Life Sciences, LLC

220 North Center Drive

North Brunswick, NJ 08902, USA

Product of USA

Tel: +1-732-743-5936

Principal Display Panel

Homeopathic Product

Honby 40

Number 503

Homeopathic Product

Caulophyllum thalictroides 200C HPUS, Sepia 30C HPUS

Helps improve prolonged amenorrhea

Quantity

96 Pills